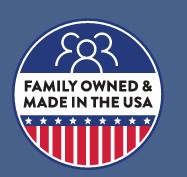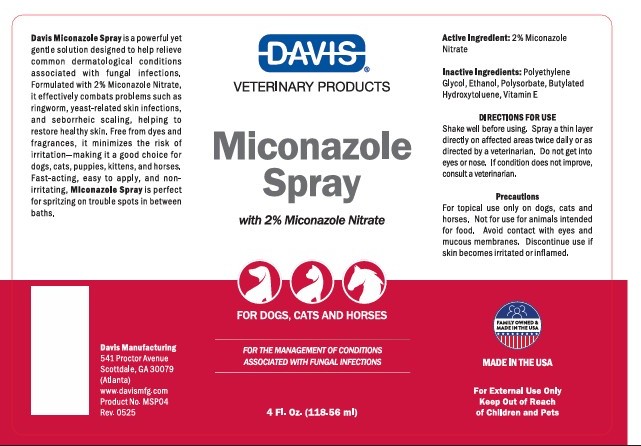 DRUG LABEL: Davis Miconazole
NDC: 62570-071 | Form: SPRAY
Manufacturer: Davis Manufacturing and Packaging Inc
Category: animal | Type: OTC ANIMAL DRUG LABEL
Date: 20251002

ACTIVE INGREDIENTS: MICONAZOLE NITRATE 2 g/100 g
INACTIVE INGREDIENTS: POLYSORBATE 20; POLYETHYLENE GLYCOL 200; ALCOHOL; BUTYLATED HYDROXYTOLUENE; .ALPHA.-TOCOPHEROL

Miconazole Spray

DESCRIPTION

Davis Miconazole Spray is a powerrful yet gentle solution designed to help relieve common dermatological conditions associated with fungal infections. Formulated with 2% Miconazole Nitrate, it effectively combats problems such as ringworm, yeast-related skin infections, and seborrheic scaling, helping to restore healthy skin. Free from dyes and fragrances, it minimizes the risk or irritation-making it a good choice for dogs, cats, puppies, kittens, and horses. Fast-acting, easy to apply, and non-irritating, Miconazole Spray is perfect for spritzing on trouble spots in between baths.

Active Ingredients: 2% Miconazole Nitrate

INACTIVE INGREDIENT

Inactive Ingredients: Polyethylene Glycol, Ethanol, Polysorbate, Butylated Hydroxytoluene, Vitamin E

DIRECTIONS FOR USE

Shake well before using. Spray a thin layer directly on affected areas twice daily or as directed by a veterinarian. Do not get into eyes or nose. If conditions do not improve, consult a veterinarian.

Precautions

For topical use only on dogs, cats, and horses. Not for use for animals intended for food. Avoid contact with eyes and mucous membranes. Discontinue use if skin becomes irritated or inflamed.

For External Use Only

Made in The USA

Davis Manufacturing and Packaging

541 Proctor Avenue

Scottdale, GA 30079

www.davismfg.com

KEEP OUT OF REACH OF CHILDREN

For External Use Only

Keep out of reach of children ans Pets

PACKAGE LABEL

Davis Veterinary Products
Miconazole Spray
With 2% Miconazole Nitrate
For Dogs, Cats, Horses
For the management of conditions associated with fungal infections

4 Fl. Oz (118.56ml)